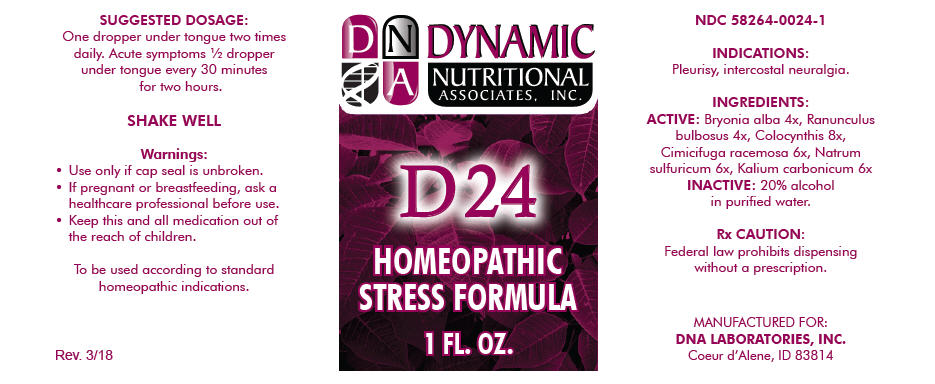 DRUG LABEL: D-24
NDC: 58264-0024 | Form: SOLUTION/ DROPS
Manufacturer: DNA Labs, Inc.
Category: homeopathic | Type: HUMAN OTC DRUG LABEL
Date: 20250113

ACTIVE INGREDIENTS: BRYONIA ALBA ROOT 4 [hp_X]/1 mL; RANUNCULUS BULBOSUS 4 [hp_X]/1 mL; CITRULLUS COLOCYNTHIS FRUIT PULP 8 [hp_X]/1 mL; BLACK COHOSH 6 [hp_X]/1 mL; SODIUM SULFATE ANHYDROUS 6 [hp_X]/1 mL; POTASSIUM CARBONATE 6 [hp_X]/1 mL
INACTIVE INGREDIENTS: ALCOHOL; WATER

D-24

NDC 58264-0024-1

INDICATIONS

PURPOSE

Pleurisy, intercostal neuralgia.

INGREDIENTS

ACTIVE

Bryonia alba 4x, Ranunculus bulbosus 4x, Colocynthis 8x, Cimicifuga racemosa 6x, Natrum sulfuricum 6x, Kalium carbonicum 6x

INACTIVE

20% alcohol in purified water.

Rx CAUTION

Federal law prohibits dispensing without a prescription.

SUGGESTED DOSAGE

One dropper under tongue two times daily. Acute symptoms ½ dropper under tongue every 30 minutes for two hours.

STORAGE AND HANDLING

SHAKE WELL

Warnings

- Use only if cap seal is unbroken.

PREGNANCY OR BREAST FEEDING

- If pregnant or breastfeeding, ask a healthcare professional before use.

KEEP OUT OF REACH OF CHILDREN

- Keep this and all medication out of the reach of children.

To be used according to standard homeopathic indications.

PRINCIPAL DISPLAY PANEL - 1 FL. OZ. Bottle Label

DYNAMIC
NUTRITIONAL
ASSOCIATES, INC.

D 24

HOMEOPATHIC
STRESS FORMULA

1 FL. OZ.